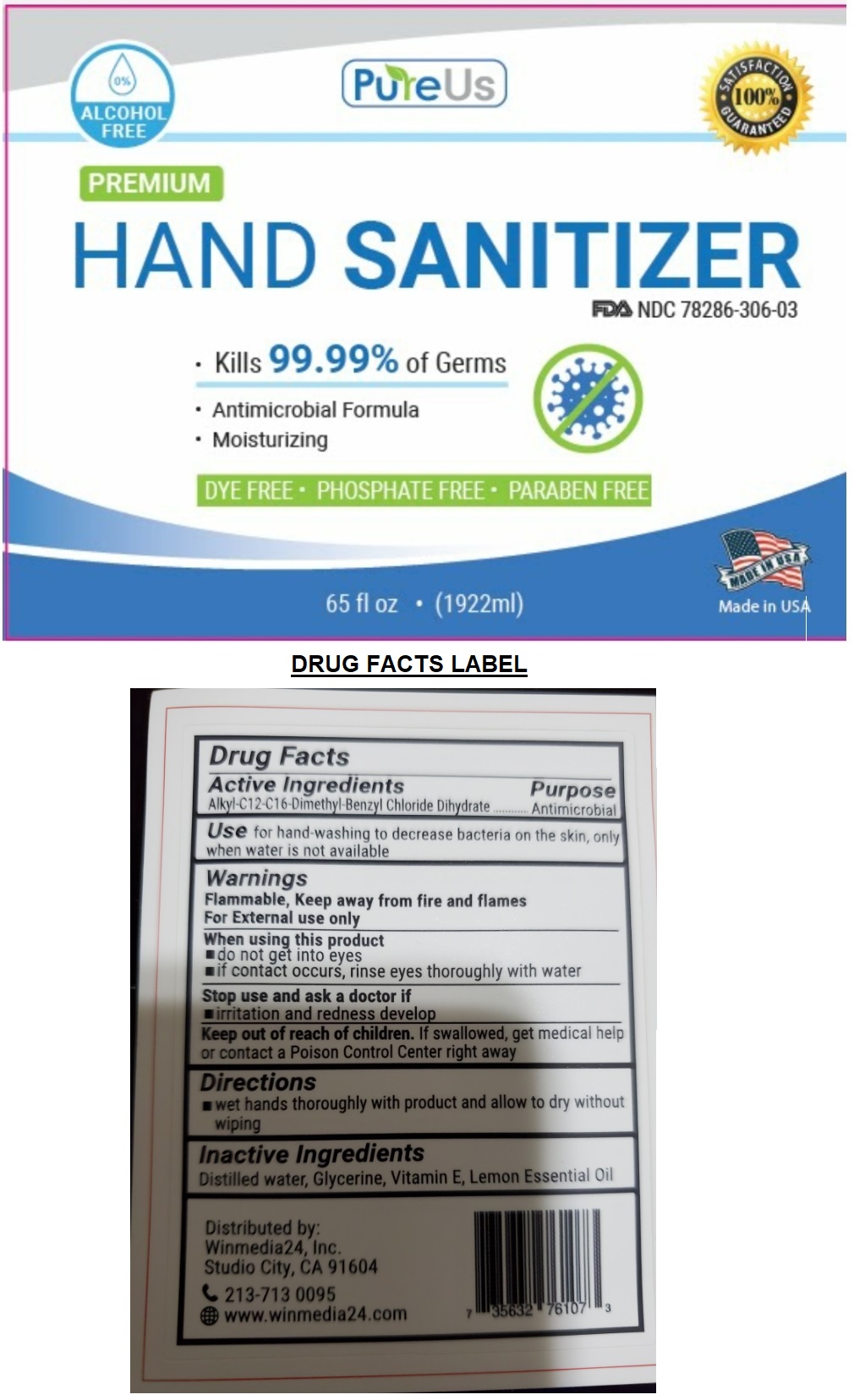 DRUG LABEL: PureUs
NDC: 78286-306 | Form: LIQUID
Manufacturer: Winmedia24
Category: otc | Type: HUMAN OTC DRUG LABEL
Date: 20200624

ACTIVE INGREDIENTS: BENZALKONIUM CHLORIDE 0.3 g/100 mL
INACTIVE INGREDIENTS: WATER; GLYCERIN; .ALPHA.-TOCOPHEROL; LEMON OIL

PureUs PREMIUM HAND SANITIZER

Active ingredients

Alkyl-C12-C16-Dimethyl-Benzyl Chloride Dihydrate

Purpose

Antimicrobial

INDICATIONS AND USAGE

Use for hand-washing to decrease bacteria on the skin, only when water is not available

Warnings

Flammable, Keep away from fire and flames

For External use only

When using this product

▪ do not get into eyes
▪ if contact occurs, rinse eyes thoroughly with water

Stop use and ask a doctor if

▪ irritation and redness develop

Keep out of reach of children. If swallowed, get medical help or contact a Poison Control Center right away

Directions

▪ wet hands thoroughly with product and allow to dry without wiping

Inactive Ingredients

Distilled water, Glycerine, Vitamin E, Lemon Essential Oil

0%

ALCOHOL FREE

- Kills 99.99% of Germs
- Antimicrobial Formula
- Moisturizing

DYE FREE • PHOSPHATE FREE • PARABEN FREE

Made in USA

SATISFACTION 100% GAURANTEED

Distributed by:

Winmedia24, Inc.

Studio City, CA 91604

213-713 0095

www.winmedia24.com